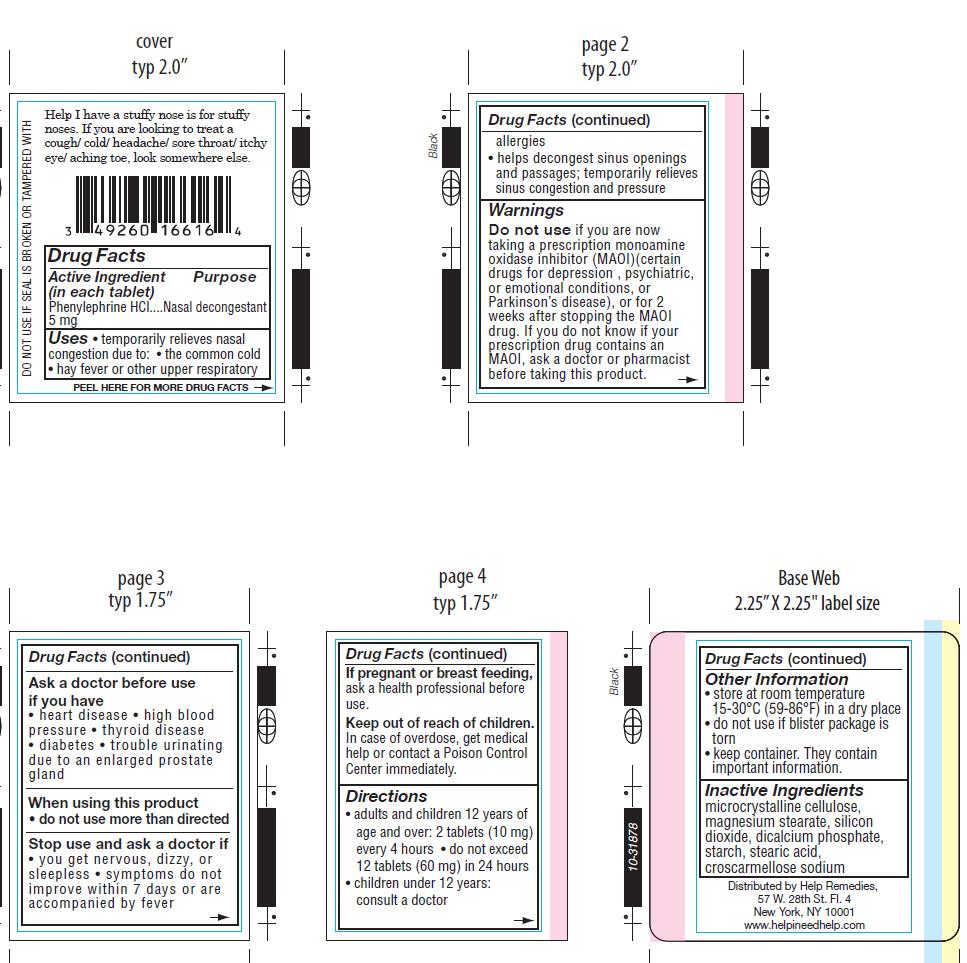 DRUG LABEL: Help I Have a Stuffy Nose
NDC: 49260-716 | Form: TABLET
Manufacturer: Help Remedies, Inc. 
Category: otc | Type: HUMAN OTC DRUG LABEL
Date: 20120709

ACTIVE INGREDIENTS: PHENYLEPHRINE HYDROCHLORIDE 5 mg/1 1
INACTIVE INGREDIENTS: CROSCARMELLOSE SODIUM; CALCIUM PHOSPHATE, DIBASIC, ANHYDROUS; MAGNESIUM STEARATE; CELLULOSE, MICROCRYSTALLINE; STARCH, CORN; SILICON DIOXIDE; STEARIC ACID

Drugs Facts

Active Ingredient.............................Purpose
(in each tablet)

Phenylephrine HCl (5 mg)............................Nasal Decongestant

Uses
Temporarily relieves nasal congestion due to:
• the common cold
• hay fever or other upper respiratory allergies
• helps decongest sinus openings and passages; temporarily relieves sinus congestion and pressure

Warnings
Do not use if you are now taking a prescription monoamine oxidase inhibitor (MAOI)(certain
drugs for depression , psychiatric, or emotional conditions, or Parkinson’s disease), or for 2
weeks after stopping the MAOI drug. If you do not know i your prescription drug contains an
MAOI, ask a doctor of pharmacist before taking this product.
Ask a doctor before use if you have
• heart disease • high blood pressure • thyroid disease • diabetes • trouble urinating due to
an enlarged prostate gland.
Stop use and ask a doctor if
• you get nervous, dizzy, or sleepless • symptoms do not improve within 7 days or are
accompanied by fever.

When using this product do not use more than directed

Keep out of reach of chidlren.

In case of accidental oversode, contact a doctor or Poison Control Center immediately.

PREGNANCY OR BREAST FEEDING

If pregnant or breast feeding, ask a health professional before use.

Directions
• adults and children 12 years of age and over: 2 tablets (10 mg) every 4 hours. • do not exceed 12 tablets (60 mg) in 24 hours

• children under 12 years of age: Consult a doctor

Other Information
• store at room temperature 15-30 degrees C (59-86 degrees F) in a dry place • do not use if blister package is torn.• keep container. They contain important information.

Inactive Ingredients
microcrystalline cellulose, magnesium stearate, silicon dioxide, dicalcium phosphate, starch, stearic acid, croscarmellose sodium

QUESTIONS

Distributed by Help Remedies,
57 W. 28th St. Fl. 4
New York, NY 10001
www.helpineedhelp.com